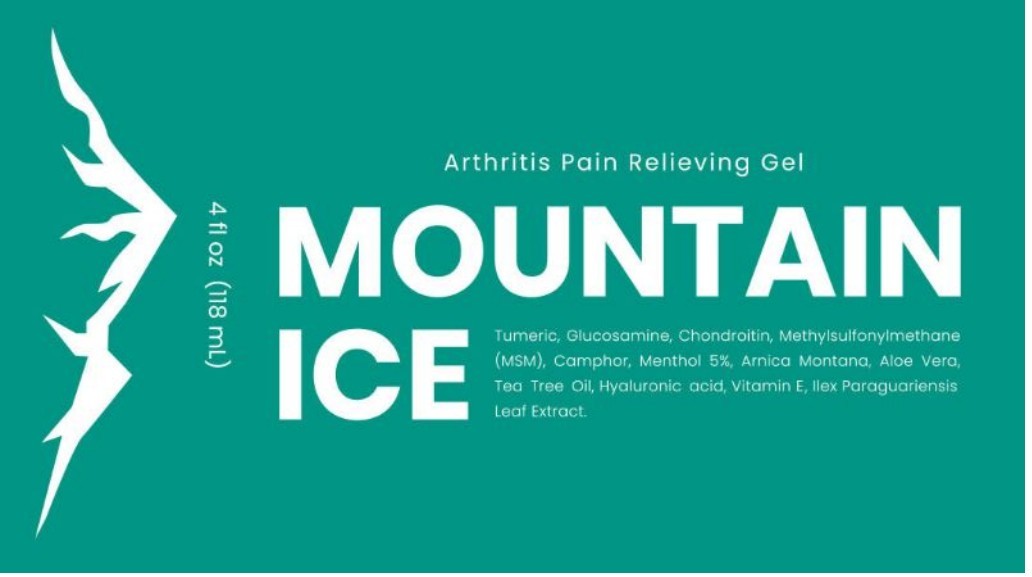 DRUG LABEL: Mountain Ice

NDC: 72793-100 | Form: GEL
Manufacturer: Mountainside Medical Equipment, Inc.
Category: otc | Type: HUMAN OTC DRUG LABEL
Date: 20250828

ACTIVE INGREDIENTS: MENTHOL, UNSPECIFIED FORM 5 g/100 mL
INACTIVE INGREDIENTS: ALOE VERA LEAF; ARNICA MONTANA FLOWER; CARBOMER HOMOPOLYMER, UNSPECIFIED TYPE; CAMPHOR OIL; TURMERIC OIL; DIMETHYL SULFONE; ETHYLHEXYLGLYCERIN; GLUCOSAMINE HYDROCHLORIDE; GLYCERIN; ILEX PARAGUARIENSIS LEAF; ISOPROPYL ALCOHOL; LIMONENE, (+)-; TEA TREE OIL; PHENOXYETHANOL; POLYSORBATE 20; PROPANEDIOL; HYALURONATE SODIUM; .ALPHA.-TOCOPHEROL ACETATE; TROLAMINE; WATER

Mountain Ice Pain Relief Gel

Active ingredients:

Menthol 5%

Purpose

External Analgesic

Uses

Temporary relief of minor aches and pains of muscles and joints associated with osteoarthritis, rheumatoid arthritis, muscle strains, and sprains

Warnings

For external use only.

Flammable; keep away from excessive heat or open flame. Avoid contact with eyes or mucous membranes.

When using this product:

- Do not apply to wounds, damaged skin, or irritated skin.
- Do not apply with other creams, ointments, sprays or liniments.
- Stop use and ask a doctor if: Conditions worsen, skin irritation develops, or condition does not improve after 7 days.

Keep out the reach of children:

If accidentally swallowed seek medical attention immediately or contact Poison Control Center right away.

Directions:

Adults and Children 2 years of age or older: Rub on the affected area evenly no more than 4 time. Children under 2 years of age: Consult with your doctor.

Inactive Ingredients:

Aloe Barbadensis Leaf Juice, Arnica Montana Flower Extract, Carbomer, Cinnamomum Camphora (Camphor) Bark Oil, Curcuma longa (Turmeric) Root Oil, Dimethyl Sulfone, Ethylhexylglycerin, Glucosamine HCl, Glycerin, Ilex Paraguariensis Leaf Extract, Isopropyl Alcohol, Limonene, Melaleuca Alternifolia (Tea Tree) Leaf Oil, Phenoxyethanol, Polysorbate 20, Propanediol, Sodium Chondroitin Sulfate, Sodium Hyaluronate, Tocopheryl Acetate, Triethanolamine, Water (Aqua), Blue 1 (CI 42090).

Package/Label Principal Display Panel – Tube Label

Arthritis Pain Relieving Gel

MOUNTAIN ICE

Tumeric, Glucosamine, Chondroitin, Methylsulfonylmethane (MSM), Camphor, Menthol 5%, Arnica Montana, Aloe Vera, Tea Tree Oil, Hyaluronic acid, Vitamin E, Ilex Paraguariensis Leaf Extract.

4 fl oz (118 mL)

Label